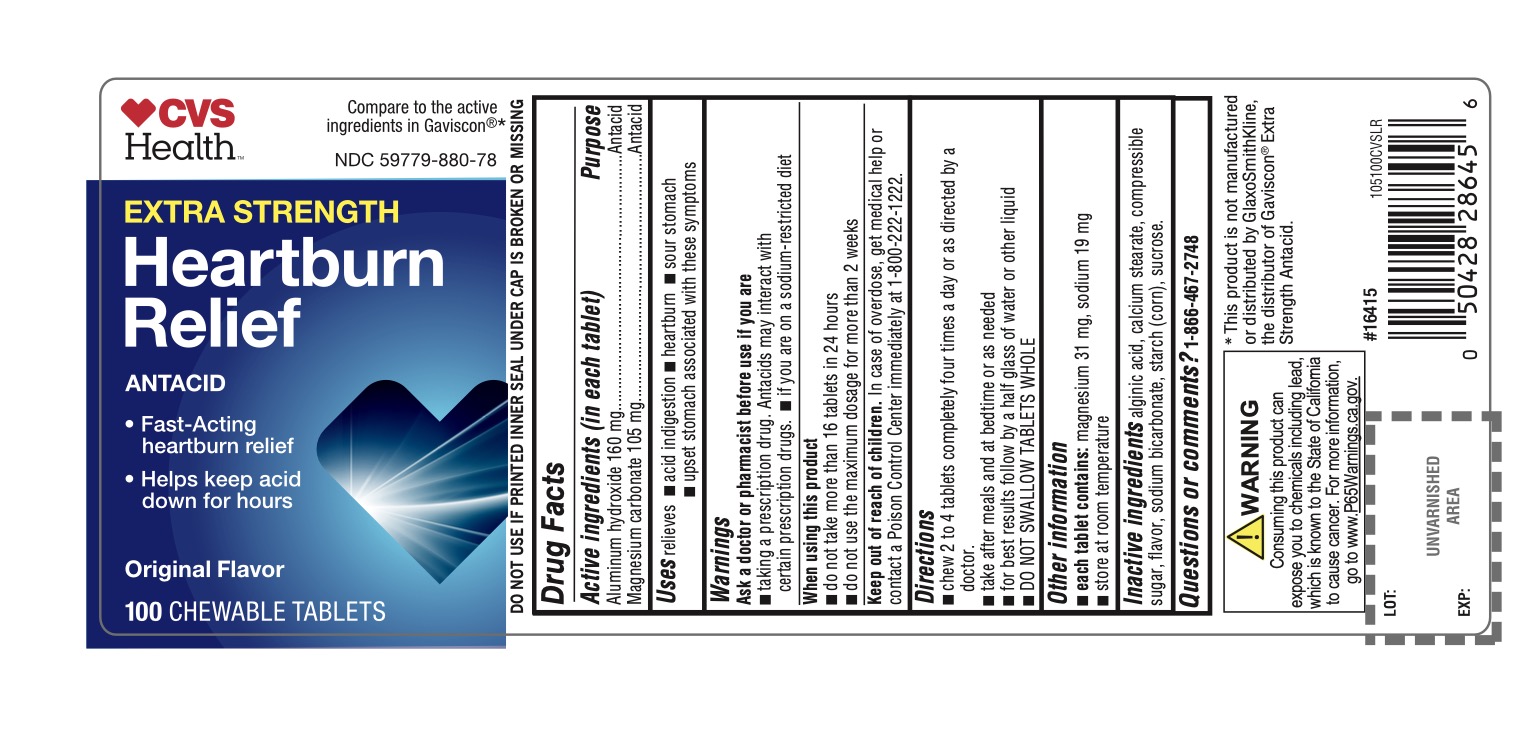 DRUG LABEL: CVS Health Extra Strength Heartburn Relief Antacid

NDC: 59779-880 | Form: TABLET, CHEWABLE
Manufacturer: CVS Pharmacy,Inc.
Category: otc | Type: HUMAN OTC DRUG LABEL
Date: 20251208

ACTIVE INGREDIENTS: ALUMINUM HYDROXIDE 160 mg/1 1; MAGNESIUM CARBONATE 105 mg/1 1
INACTIVE INGREDIENTS: ALGINIC ACID; CALCIUM STEARATE; CORN SYRUP; SODIUM BICARBONATE; STARCH, CORN; SUCROSE

CVS Health Extra Strength Heartburn Relief Antacid Chewable Tablets Original Flavor 100 Count

Active ingredients (in each tablet)

Aluminum hydroxide 160 mg

Magnesium carbonate 105 mg

Purpose

Antacid

Antacid

Uses

relieves

- acid indigestion
- heartburn
- sour stomach
- upset stomach associated with these symptoms

Warnings

Ask a doctor or pharmacist before use if you are

- taking a prescription drug. Antacids may interact with certain prescription drugs
- on a sodium-restricted diet

When using this product

- do not take more than 16 tablets in 24 hours
- do not use the maximum dosage for more than 2 weeks

Keep out of reach of children.

In case of overdose, get medical help or contact a Poison Control Center immediately.1-800-222-1222

Directions

- chew 2 to 4 tablets four times a day or as directed by a doctor
- take after meals and at bedtime or as needed
- for best results follow by a half glass of water or other liquid
- DO NOT SWALLOW WHOLE

Other information

- each tablet contains:sodium 19 mg, magnesium 31 mg
- Store at up to 25°C (77°F) in a dry place

Inactive ingredients

alginic acid, calcium stearate, compressible sugar, flavor, sodium bicarbonate, starch (corn), sucrose.

Questions or comments?

1-866-467-2748

Principal Display Panel

CVS Health™

Compare to the active ingredients in Gaviscon®*

NDC 59779-880-78

EXTRA STRENGTH

Heartburn Relief

ANTACID

- Fast-Acting heartburn relief
- Helps keep acid down for hours

Original Flavor

100 CHEWABLE TABLETS

Do not use if printed seal under cap is torn or missing

Distributed by:

CVS Pharmacy, Inc.

One CVS Drive,

Woonsocket, RI 02895

©2016 CVS/pharmacy

CVS.com®

1-800-SHOP CVS

Made in the USA V-16415

CVS®Quality

Money Back Guarantee

*This product is not manufactured or distributed by GlaxoSmithKline, the distributor of Gaviscon® Extra Strength.

.